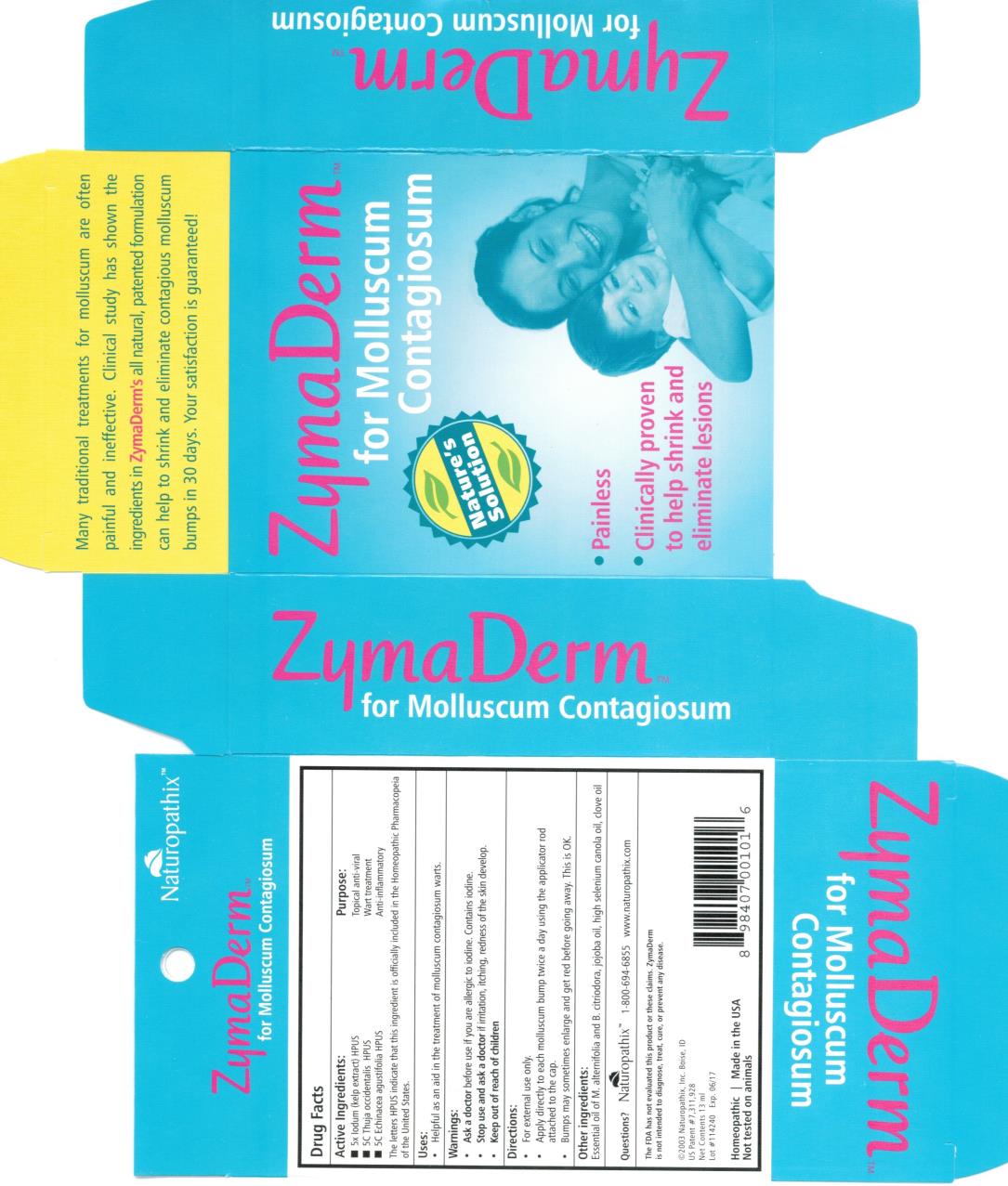 DRUG LABEL: ZymaDerm
NDC: 69163-4131 | Form: LIQUID
Manufacturer: Naturopathix, Inc.
Category: homeopathic | Type: HUMAN OTC DRUG LABEL
Date: 20130422

ACTIVE INGREDIENTS: IODINE 5 [hp_X]/13 mL; THUJA OCCIDENTALIS WHOLE 5 [hp_C]/13 mL; ECHINACEA, UNSPECIFIED 5 [hp_C]/13 mL
INACTIVE INGREDIENTS: TEA TREE OIL; BACKHOUSIA CITRIODORA WHOLE; JOJOBA OIL; CANOLA OIL; CLOVE OIL

ZymaDerm

Drug Facts

Active Ingredient

5x Iodum (kelp extract)

Purpose

Topical anti-viral

Active Ingredient

5C Thuja

Purpose

Wart treatment

Active Ingredient

5C Echinacea

Purpose

Anti-inflammatory

Uses:

Helpful as an aid in the treatment of molluscum contagiosum warts.

Directions:

Apply twice a day using the applicator rod. Minimize contact with normal skin as ZymaDerm™ can be drying over a period of weeks.

KEEP OUT OF REACH OF CHILDREN.

NOT TO BE TAKEN INTERNALLY. CONTAINS IODINE. IF YOU ARE ALLERGIC TO IODINE CONSULT YOUR PHYSICIAN PRIOR TO USE.

Discontinue if any redness of the surrounding skin develops, or for any discomfort. If there is any development you are unsure about, stop ZymaDerm™ and call us at 1-800-694-6855. If swallowed, give water. Flush with water if accidental contact with eyes occurs. Spills may be cleaned with rubbing alcohol.

Other Ingredients:

Essential oil of M. alternifolia and B. citriodora, Jojoba oil, high selenium canola oil, clove oil.

Distributed by Naturopathix, Inc. Boise, ID 1-800-694-6855

Net Contents: 13ml

©2003 Naturopathix, Inc. Boise, ID. All rights reserved. Homeopathic

US Patent #7,311,928

Principal Display Panel

ZymaDerm TM

For Molluscum

Contagiosum